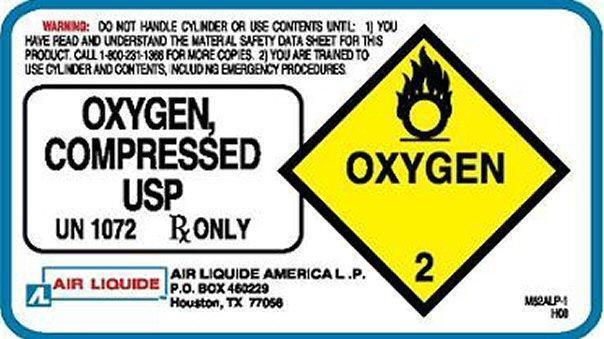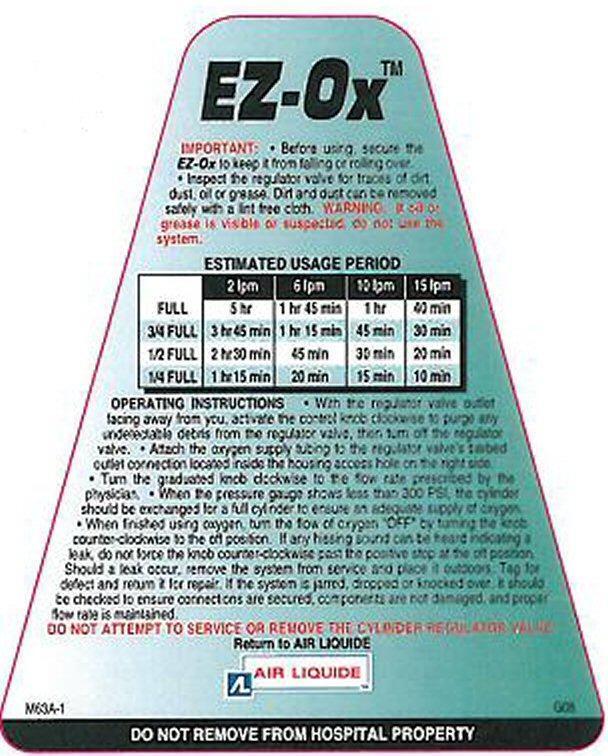 DRUG LABEL: EZ-OX
NDC: 10671-100 | Form: GAS
Manufacturer: Air Liquide America L.P.
Category: prescription | Type: HUMAN PRESCRIPTION DRUG LABEL
Date: 20150219

ACTIVE INGREDIENTS: OXYGEN 99 L/100 L

OXYGEN COMPRESSED USP Label

WARNING: DO NOT HANDLE CYLINDER OR USE CONTENTS UNTIL 1) YOU HAVE READ AND UNDERSTAND THE MATERIAL SAFETY DATA SHEET FOR THIS PRODUCT. CALL 1-800-231-1366 FOR MORE COPIES. 2) YOU ARE TRAINED TO USE CYLINDER AND CONTENTS, INCLUDING EMERGENCY PROCEDURES.

OXYGEN COMPRESSED USP OXYGEN 2

UN 1072 Rx ONLY

AIR LIQUIDE

AIR LIQUIDE AMERICA L.P.
P.O. BOX 460229
Houston, TX 77056

M62ALP-1 H08

EZ-OX Label

EZ-OX™

IMPORTANT: · Before using secure the EZ-OX to keep it from falling or rolling over. · Inspect the regulator valve for traces of dirt, dust, oil or grease. Dirt and dust can be removed safely with a lint free cloth.

WARNING: If oil or grease is visible or suspected do not use the system.

OPERATING INSTRUCTIONS · With the regulator valve outlet facing away from you, activate the control knob clockwise to purge any undetectable debris from the regulator valve, then turn off the regulator valve · Attach the oxygen supply tubing to the regulator valve's barbed outlet connection located inside the housing access hole on the right side. · Turn the graduated knob clockwise to the flow rate prescribed by the physician · When the pressure gauge shows 300 PSI, the cylinder should be exchanged for a full cylinder to ensure an adequate supply of oxygen · When finished using oxygen, turn the flow of oxygen to "OFF" by turning the knob counter-clockwise to the off position. If any hissing sound can be heard indicating a leak, do not force the knob counter-clockwise past the positive stop at the off position. Should a leak occur, remove the system from service and place it outdoors. Tag for defect and return it for repair. If the system is jarred, dropped or knocked over, it should be checked to ensure connections are secured, components are not damaged, and proper flow rate is maintained.

DO NOT ATTEMPT TO SERVICE OR REMOVE THE CYLINDER REGULATOR VALVE

Return to AIR LIQUIDE
AIR LIQUIDE

M63A-1

D NOT REMOVE FROM HOSPITAL PROPERTY